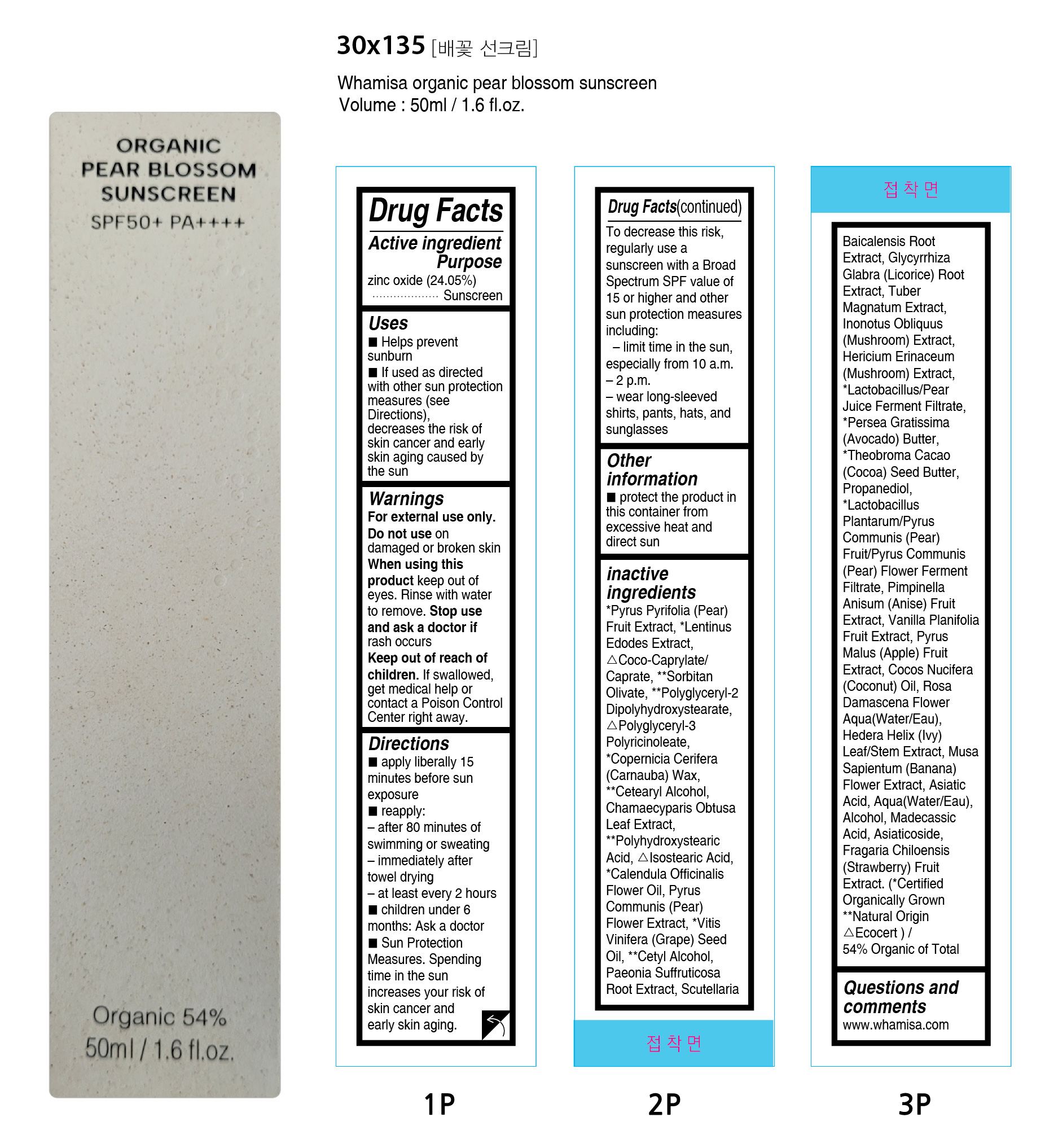 DRUG LABEL: WHAMISA ORGANIC PEAR BLOSSOM SUNSCREEN
NDC: 73391-0101 | Form: CREAM
Manufacturer: ENS KOREA Co., Ltd.
Category: otc | Type: HUMAN OTC DRUG LABEL
Date: 20250512

ACTIVE INGREDIENTS: ZINC OXIDE 24.05 g/100 g
INACTIVE INGREDIENTS: COCO-CAPRYLATE/CAPRATE 11.1 g/100 g

DOSAGE AND ADMINISTRATION

• Helps prevent sunburn
• If used as directed with other sun protection measures (see Directions),
decreases the risk of skin cancer and early skin aging caused by the sun

WARNINGS

For external use only

Do not use
• on damaged or broken skin

When using this product
• keep out of eyes. Rinse with water to remove.

Stop use and ask a doctor if
• rash occurs

Keep out of reach of children.
If swallowed, get medical help or contact a Poison Control Center right away.

INACTIVE INGREDIENT

*Pyrus Pyrifolia (Pear) Fruit Extract, *Lentinus Edodes Extract, △Coco-Caprylate/Caprate, **Sorbitan Olivate, **Polyglyceryl-2 Dipolyhydroxystearate, △Polyglyceryl-3 Polyricinoleate, *Copernicia Cerifera (Carnauba) Wax, **Cetearyl Alcohol, Chamaecyparis Obtusa Leaf Extract, **Polyhydroxystearic Acid, △Isostearic Acid, *Calendula Officinalis Flower Oil, Pyrus Communis (Pear) Flower Extract, *Vitis Vinifera (Grape) Seed Oil, **Cetyl Alcohol, Paeonia Suffruticosa Root Extract, Scutellaria Baicalensis Root Extract, Glycyrrhiza Glabra (Licorice) Root Extract, Tuber Magnatum Extract, Inonotus Obliquus (Mushroom) Extract, Hericium Erinaceum (Mushroom) Extract, *Lactobacillus/Pear Juice Ferment Filtrate, *Persea Gratissima (Avocado) Butter, *Theobroma Cacao (Cocoa) Seed Butter, Propanediol, *Lactobacillus Plantarum/Pyrus Communis (Pear) Fruit/Pyrus Communis (Pear) Flower Ferment Filtrate, Pimpinella Anisum (Anise) Fruit Extract, Vanilla Planifolia Fruit Extract, Pyrus Malus (Apple) Fruit Extract, Cocos Nucifera (Coconut) Oil, Rosa Damascena Flower Aqua(Water/Eau), Hedera Helix (Ivy) Leaf/Stem Extract, Musa Sapientum (Banana) Flower Extract, Asiatic Acid, Aqua(Water/Eau), Alcohol, Madecassic Acid, Asiaticoside, Fragaria Chiloensis (Strawberry) Fruit Extract. (*Certified Organically Grown **Natural Origin △Ecocert) / 54% Organic of Total

INDICATIONS AND USAGE

• apply liberally 15 minutes before sun exposure
• reapply:
– after 80 minutes of swimming or sweating
– immediately after towel drying
– at least every 2 hours
• children under 6 months: Ask a doctor

PURPOSE

• Helps prevent sunburn
• If used as directed with other sun protection measures (see Directions),
decreases the risk of skin cancer and early skin aging caused by the sun

KEEP OUT OF REACH OF CHILDREN

If swallowed, get medical help or contact a Poison Control Center right away.